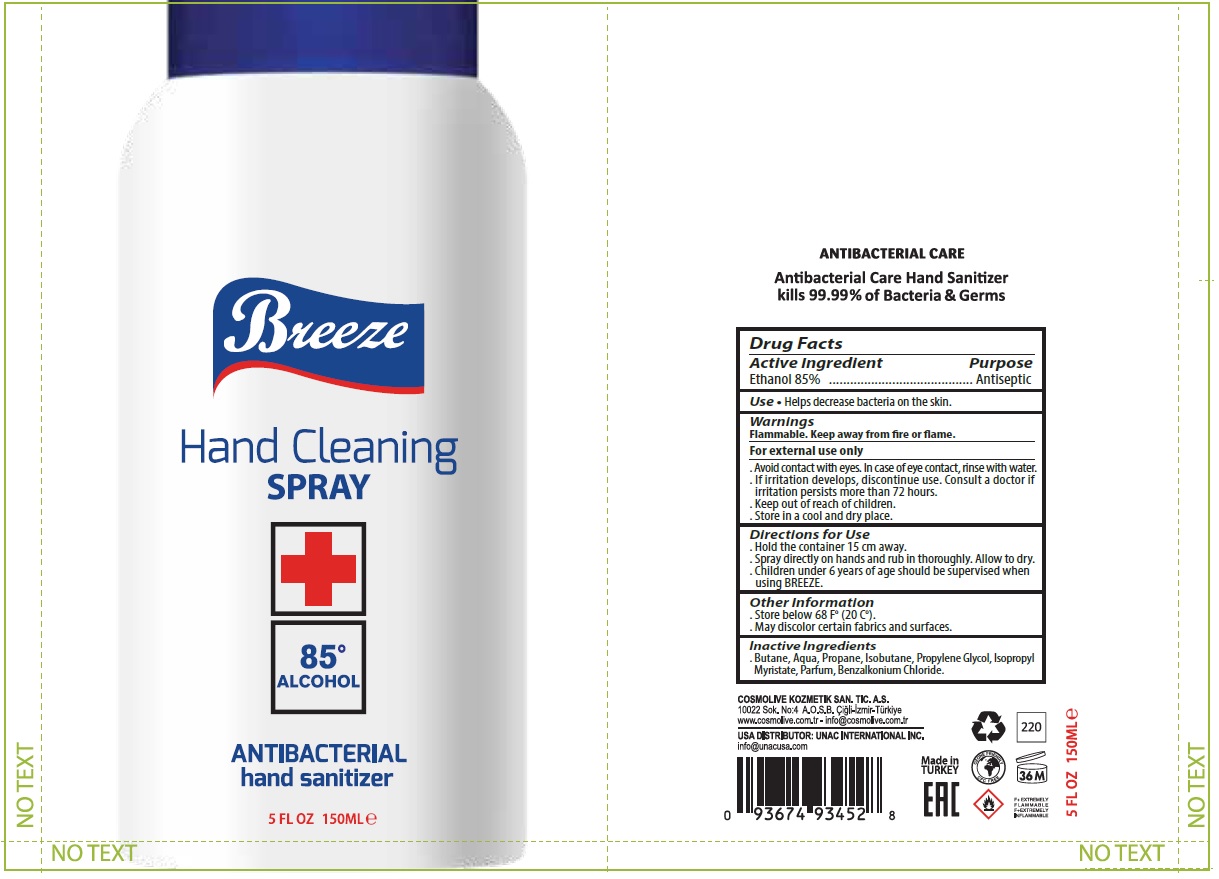 DRUG LABEL: BREEZE ANTIBACTERIAL 150 ML
NDC: 74955-022 | Form: SPRAY
Manufacturer: COSMOLIVE KOZMETIK SANAYI VE TICARET ANONIM SIRKETI
Category: otc | Type: HUMAN OTC DRUG LABEL
Date: 20200520

ACTIVE INGREDIENTS: ALCOHOL 85 mL/100 mL
INACTIVE INGREDIENTS: BUTANE; WATER; PROPANE; ISOBUTANE; PROPYLENE GLYCOL; ISOPROPYL MYRISTATE; BENZALKONIUM CHLORIDE

Breeze ANTIBACTERIAL hand sanitizer

Active Ingredient

Ethanol 85%

Purpose

Antiseptic

INDICATIONS AND USAGE

Use • Helps decrease bacteria on the skin.

Warnings

Flammable. Keep away from fire or flame.

For external use only

- Avoid contact with eyes. In case of eye contact, rinse with water.
- If irritation develops, discontinue use. Consult a doctor if irritation persists more than 72 hours.
- Store in cool and dry place.

- Keep out of reach of children

Directions for use

- Hold the container 15 cm away.
- Spray directly on hands and rub in thoroughly. Allow to dry.
- Children under 6 years of age should be supervised when using BREEZE.

Other Information

- Store between 68°F (20°C).
- May discolor certain fabrics and surfaces.

Inactive Ingredients

- Butane, Aqua, Propane, Isobutane, Propylene Glycol, Isopropyl Myristate, Parfum, Benzalkonium Chloride.

Hand Cleaning SPRAY +

ANTIBACTERIAL Hand Sanitizer

ANTIBACTERIAL CARE

Antibacterial Care Hand Sanitizer

kills 99.99% of Bacteria and Germs

COSMOLIVE KOZMETIK SAN. TIC. A.S.

10022 Sok. No:4 A.O.S.B. Çiğli-İzmir-Türkiye

www.cosmolive.com.tr - info@cosmolive.com.tr

USA DISTRIBUTOR: UNAC INTERNATIONAL INC.

info@unacusa.com

Made in TURKEY

EAC